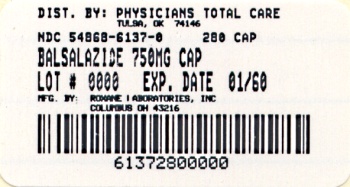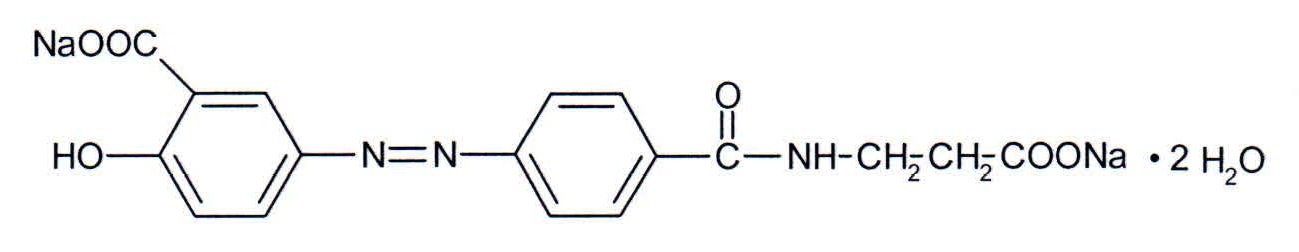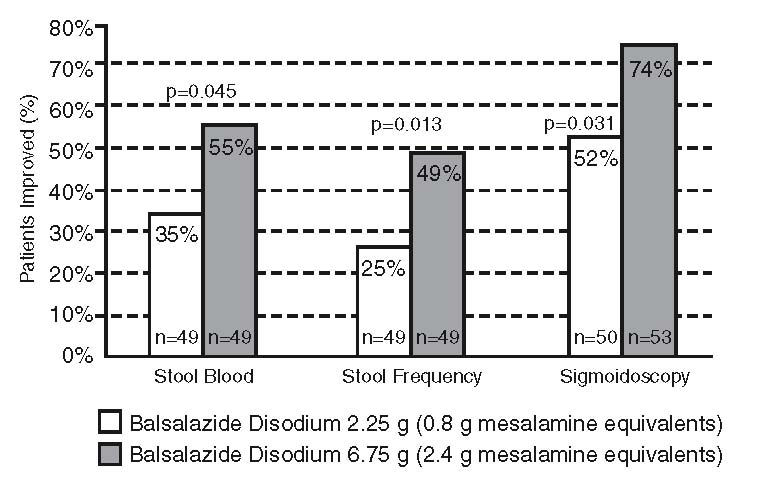 DRUG LABEL: Balsalazide Disodium
NDC: 54868-6137 | Form: CAPSULE
Manufacturer: Physicians Total Care, Inc.
Category: prescription | Type: HUMAN PRESCRIPTION DRUG LABEL
Date: 20100521

ACTIVE INGREDIENTS: BALSALAZIDE DISODIUM 750 mg/1 1
INACTIVE INGREDIENTS: AMMONIA; SILICON DIOXIDE; FD&C BLUE NO. 1; FD&C RED NO. 40; FD&C YELLOW NO. 6; GELATIN; FERROSOFERRIC OXIDE; ISOPROPYL ALCOHOL; MAGNESIUM STEARATE; BUTYL ALCOHOL; PROPYLENE GLYCOL; SHELLAC; TITANIUM DIOXIDE

HIGHLIGHTS OF PRESCRIBING INFORMATION

These highlights do not include all the information needed to use Balsalazide Disodium Capsules, 750 mg safely and effectively. See full prescribing information for Balsalazide Disodium Capsules. Balsalazide Disodium Capsules for oral use
Initial U.S. Approval: 2000

RECENT MAJOR CHANGES

Drug Interactions (7) 2/2007

Postmarketing Experience (6.2) 5/2008

1 INDICATIONS AND USAGE

- Balsalazide Disodium Capsules are a locally acting aminosalicylate indicated for the treatment of mildly to moderately active ulcerative colitis in adults. (1)
- Safety and effectiveness of Balsalazide Disodium Capsules beyond 12 weeks in adults have not been established. (1)

2 DOSAGE AND ADMINISTRATION

- Adult dose is three 750 mg balsalazide capsules 3 times a day (6.75 g/day) with or without food for 8 weeks. Some adult patients required treatment for up to 12 weeks. (2.1)
- Capsules may be swallowed whole or may be opened and sprinkled on applesauce, then chewed or swallowed immediately. (2.2, 12.3)

3 DOSAGE FORMS AND STRENGTHS

Capsules: 750 mg (3)

4 CONTRAINDICATIONS

Patients with hypersensitivity to salicylates or to any of the components of Balsalazide Disodium Capsules or balsalazide metabolites. Hypersensitivity reactions may include, but are not limited to the following: anaphylaxis, bronchospasm, and skin reaction. (4)

5 WARNINGS AND PRECAUTIONS

- Exacerbation of the symptoms of ulcerative colitis was reported in adult patients. Observe patients closely for worsening of these symptoms while on treatment. (5.1)
- Prolonged gastric retention of balsalazide may occur in patients with pyloric stenosis. (5.2)

6 ADVERSE REACTIONS

Most common adverse reactions in adults (incidence ≥3% are headache, abdominal pain, diarrhea, nausea, vomiting, respiratory infection, and arthralgia. Adverse reactions in children were similar. (6.1)

To report SUSPECTED ADVERSE REACTIONS, contact Roxane Laboratories, Inc. at 1-800-962-8364 or FDA at 1-800-FDA-1088 or www.fda.gov/medwatch.

7 DRUG INTERACTIONS

In an in vitro study using human liver microsomes, balsalazide and its metabolites were not shown to inhibit the major CYP enzymes evaluated (CYP1A2, CYP2C9, CYP2C19, CYP2D6, and CYP3A4/5). (7)

8 USE IN SPECIFIC POPULATIONS

Renal Impairment: Use balsalazide with caution in patients with a history of renal disease. (5.3)

Pediatric: Pediatric use information is protected by marketing exclusivity. (8.4)

FULL PRESCRIBING INFORMATION

1 INDICATIONS AND USAGE

Balsalazide Disodium Capsules are indicated for the treatment of mildly to moderately active ulcerative colitis in adults. Safety and effectiveness of Balsalazide Disodium Capsules beyond 12 weeks in adults have not been established.

2 DOSAGE AND ADMINISTRATION

2.1 Adult Dose

For treatment of active ulcerative colitis in adult patients, the usual dose is three 750 mg balsalazide capsules to be taken 3 times a day (6.75 g per day) for up to 8 weeks. Some patients in the adult clinical trials required treatment for up to 12 weeks.

2.2 Administration Alternatives

Balsalazide capsules may also be administered by carefully opening the capsule and sprinkling the capsule contents on applesauce. The entire drug/applesauce mixture should be swallowed immediately; the contents may be chewed, if necessary, since contents of balsalazide are NOT coated beads/granules. Patients should be instructed not to store any drug/applesauce mixture for future use.

If the capsules are opened for sprinkling, color variation of the powder inside the capsules ranges from orange to yellow and is expected due to color variation of the active pharmaceutical ingredient.

Teeth and/or tongue staining may occur in some patients who use balsalazide in sprinkle form with food.

3 DOSAGE FORMS AND STRENGTHS

Balsalazide Disodium Capsules are available as light orange opaque capsules containing 750 mg balsalazide disodium and "54 795" imprinted in black ink on the cap and body, containing a yellow-orange powder.

4 CONTRAINDICATIONS

Patients with hypersensitivity to salicylates or to any of the components of Balsalazide Disodium Capsules or balsalazide metabolites. Hypersensitivity reactions may include, but are not limited to the following: anaphylaxis, bronchospasm, and skin reaction.

5 WARNINGS AND PRECAUTIONS

5.1 Exacerbations of Ulcerative Colitis

In the adult clinical trials, 3 out of 259 patients reported exacerbation of the symptoms of ulcerative colitis.

Observe patients closely for worsening of these symptoms while on treatment.

5.2 Pyloric Stenosis

Patients with pyloric stenosis may have prolonged gastric retention of balsalazide capsules.

5.3 Renal

Renal toxicity has been observed in animals and patients given other mesalamine products. Therefore, caution should be exercised when administering balsalazide to patients with known renal dysfunction or a history of renal disease. [See 13 NONCLINICAL TOXICOLOGY (13.2)]

6 ADVERSE REACTIONS

6.1 Clinical Studies Experience

Because clinical studies are conducted under widely varying conditions, adverse reaction rates observed in the clinical studies of a drug cannot be directly compared to rates in the clinical studies of another drug and may not reflect the rates observed in practice.

Adult Ulcerative Colitis

During clinical development, 259 adult patients with active ulcerative colitis were exposed to 6.75 g/day balsalazide in 4 controlled trials.

In the 4 controlled clinical trials patients receiving a balsalazide dose of 6.75 g/day most frequently reported the following adverse reactions: headache (8%), abdominal pain (6%), diarrhea (5%), nausea (5%), vomiting (4%), respiratory infection (4%), and arthralgia (4%). Withdrawal from therapy due to adverse reactions was comparable among patients on balsalazide and placebo.

Adverse reactions reported by 1% or more of patients who participated in the 4 well-controlled, Phase 3 trials are presented by treatment group (Table 1).

The number of placebo patients (35), however, is too small for valid comparisons. Some adverse reactions, such as abdominal pain, fatigue, and nausea were reported more frequently in women than in men. Abdominal pain, rectal bleeding, and anemia can be part of the clinical presentation of ulcerative colitis.

Table 1: Adverse Reactions Occurring In ≥ 1% of Adult Balsalazide Patients In Controlled Trials
Adverse Reaction | Balsalazide 6.75 g/day (N=259) | Placebo (N=35)
Abdominal Pain | 16 (6%) | 1 (3%)
Diarrhea | 14 (5%) | 1 (3%)
Arthralgia | 9 (4%) | 0%
Rhinitis | 6 (2%) | 0%
Insomnia | 6 (2%) | 0%
Fatigue | 6 (2%) | 0%
Flatulence | 5 (2%) | 0%
Fever | 5 (2%) | 0%
Dyspepsia | 5 (2%) | 0%
Pharyngitis | 4 (2%) | 0%
Coughing | 4 (2%) | 0%
Anorexia | 4 (2%) | 0%
Urinary Tract Infection | 3 (1%) | 0%
Myalgia | 3 (1%) | 0%
Flu-Like Disorder | 3 (1%) | 0%
Dry Mouth | 3 (1%) | 0%
Cramps | 3 (1%) | 0%
Constipation | 3 (1%) | 0%

6.2 Postmarketing Experience

The following adverse reactions have been identified during post-approval use of balsalazide in clinical practice: myocarditis, pericarditis, vasculitis, pruritus, pleural effusion, pneumonia (with and without eosinophilia), alveolitis, renal failure,interstitial nephritis, pancreatitis, and alopecia.

Because these reactions are reported voluntarily from a population of unknown size, it is not always possible to reliably estimate their frequency or establish a causal relationship to drug exposure. These adverse reactions have been chosen for inclusion due to a combination of seriousness, frequency of reporting, or potential causal connection to balsalazide.

Hepatic

Postmarketing adverse reactions of hepatotoxicity have been reported for products which contain (or are metabolized to) mesalamine, including elevated liver function tests (SGOT/AST, SGPT/ALT, GGT, LDH, alkaline phosphatase, bilirubin), jaundice, cholestatic jaundice, cirrhosis, hepatocellular damage including liver necrosis and liver failure. Some of these cases were fatal; however, no fatalities associated with these adverse reactions were reported in balsalazide clinical trials. One case of Kawasaki-like syndrome which included hepatic function changes was also reported, however, this adverse reaction was not reported in balsalazide clinical trials.

7 DRUG INTERACTIONS

In an in vitro study using human liver microsomes, balsalazide and its metabolites [5-aminosalicylic acid (5-ASA), N-acetyl-5-aminosalicylic acid (N-Ac-5-ASA), 4-aminobenzoyl-ß-alanine (4-ABA) and N-acetyl-4-aminobenzoyl-ß–alanine (N-Ac-4-ABA)] were not shown to inhibit the major CYP enzymes evaluated (CYP1A2, CYP2C9, CYP2C19, CYP2D6, and CYP3A4/5). Therefore, balsalazide and its metabolites are not expected to inhibit the metabolism of other drugs which are substrates of CYP1A2, CYP2C9, CYP2C19, CYP2D6, or CYP3A4/5.

8 USE IN SPECIFIC POPULATIONS

8.1 Pregnancy

Pregnancy Category B. Reproduction studies were performed in rats and rabbits at oral doses up to 2 g/kg/day, 2.4 and 4.7 times the recommended human dose based on body surface area for the rat and rabbit, respectively, and revealed no evidence of impaired fertility or harm to the fetus due to balsalazide disodium. There are, however, no adequate and well-controlled studies in pregnant women. Because animal reproduction studies are not always predictive of human response, this drug should be used during pregnancy only if clearly needed.

8.3 Nursing Mothers

It is not known whether balsalazide disodium is excreted in human milk. Because many drugs are excreted in human milk, caution should be exercised when balsalazide is administered to a nursing woman.

8.4 Pediatric Use

Pediatric use information is protected by marketing exclusivity.

10 OVERDOSAGE

No case of overdose has occurred with balsalazide. A 3-year-old boy is reported to have ingested 2 g of another mesalamine product. He was treated with ipecac and activated charcoal with no adverse reactions.

If an overdose occurs with balsalazide, treatment should be supportive, with particular attention to correction of electrolyte abnormalities.

11 DESCRIPTION

Each Balsalazide Disodium Capsule contains 750 mg of balsalazide disodium, a prodrug that is enzymatically cleaved in the colon to produce mesalamine (5-aminosalicylic acid or 5-ASA), an anti-inflammatory drug. Each capsule of balsalazide (750 mg) is equivalent to 267 mg of mesalamine. Balsalazide disodium has the chemical name (E)-5-[[-4-[[(2-carboxyethyl) amino]carbonyl] phenyl]azo]-2-hydroxybenzoic acid, disodium salt, dihydrate. Its structural formula is:

Molecular Weight: 437.32

Molecular Formula: C17H13N3O6Na2•2H2O

Balsalazide disodium is a stable, odorless orange to yellow microcrystalline powder. It is freely soluble in water and isotonic saline, sparingly soluble in methanol and ethanol, and practically insoluble in all other organic solvents.

Inactive Ingredients: Each hard gelatin capsule contains ammonium hydroxide, colloidal silicon dioxide, FD&C Blue #1, FD&C Red #40, FD&C Yellow #6, gelatin, iron oxide black, isopropyl alcohol, magnesium stearate, n-butyl alcohol, propylene glycol, shellac, and titanium dioxide. The sodium content of each capsule is approximately 79 mg.

12 CLINICAL PHARMACOLOGY

12.1 Mechanism of Action

Balsalazide disodium is delivered intact to the colon where it is cleaved by bacterial azoreduction to release equimolar quantities of mesalamine, which is the therapeutically active portion of the molecule, and the 4-aminobenzoyl-ß-alanine carrier moiety. The carrier moiety released when balsalazide disodium is cleaved is only minimally absorbed and is largely inert.

The mechanism of action of 5-ASA is unknown, but appears to be local to the colonic mucosa rather than systemic. Mucosal production of arachidonic acid metabolites, both through the cyclooxygenase pathways, i.e., prostanoids, and through the lipoxygenase pathways, i.e., leukotrienes and hydroxyeicosatetraenoic acids, is increased in patients with chronic inflammatory bowel disease, and it is possible that 5-ASA diminishes inflammation by blocking production of arachidonic acid metabolites in the colon.

12.3 Pharmacokinetics

Balsalazide capsules contain a powder of balsalazide disodium that is insoluble in acid and designed to be delivered to the colon as the intact prodrug. Upon reaching the colon, bacterial azoreductases cleave the compound to release 5-ASA, the therapeutically active portion of the molecule, and 4-aminobenzoyl-ß-alanine. The 5-ASA is further metabolized to yield N-acetyl-5-aminosalicylic acid (N-Ac-5-ASA), a second key metabolite.

Absorption

The plasma pharmacokinetics of balsalazide and its key metabolites from a crossover study in healthy volunteers are summarized in Table 2. In this study, a single oral dose of balsalazide 2.25 g was administered to healthy volunteers as intact capsules (3 x 750 mg) under fasting conditions, as intact capsules (3 x 750 mg) after a high-fat meal, and unencapuslated (3 x 750 mg) as sprinkles on applesauce.

Table 2: Plasma Pharmacokinetics for Balsalazide and Key Metabolites (5-ASA and N-Ac-5-ASA) with Administration of Balsalazide Following a Fast, a High-Fat Meal, and Drug Contents Sprinkled on Applesauce (Mean ± SD)
 | Fasting (N=17) | High-Fat Meal (N=17) | Sprinkled (N=17)
Cmax (mcg/mL)
Balsalazide | 0.51 ± 0.32 | 0.45 ± 0.39 | 0.21 ± 0.12
5-ASA | 0.22 ± 0.12 | 0.11 ± 0.136 | 0.29 ± 0.17
N-Ac-5-ASA | 0.88 ± 0.39 | 0.64 ± 0.534 | 1.04 ± 0.57
AUClast (mcg·hr/mL)
Balsalazide | 1.35 ± 0.73 | 1.52 ± 1.01 | 0.87 ± 0.48
5-ASA | 2.59 ± 1.46 | 2.1 ± 2.58 | 2.99 ± 1.7
N-Ac-5-ASA | 17.8 ± 8.14 | 17.7 ± 13.7 | 20 ± 11.4
Tmax (h)
Balsalazide | 0.8 ± 0.85 | 1.2 ± 1.11 | 1.6 ± 0.44
5-ASA | 8.2 ± 1.98 | 22 ± 8.23 | 8.7 ± 1.99
N-Ac-5-ASA | 9.9 ± 2.49 | 20.2 ± 8.94 | 10.8 ± 5.39

A relatively low systemic exposure was observed under all three administered conditions (fasting, fed with high-fat meal, sprinkled on applesauce), which reflects the variable, but minimal absorption of balsalazide disodium and its metabolites. The data indicate that both Cmax and AUClast were lower, while Tmax was markedly prolonged, under fed (high-fat meal) compared to fasted conditions. Moreover, the data suggest that dosing balsalazide disodium as a sprinkle or as a capsule provides highly variable, but relatively similar mean pharmacokinetic parameter values. No inference can be made as to how the systemic exposure differences of balsalazide and its metabolites in this study might predict the clinical efficacy under different dosing conditions (i.e., fasted, fed with high-fat meal, or sprinkled on applesauce) since clinical efficacy after balsalazide disodium administration is presumed to be primarily due to the local effects of 5-ASA on the colonic mucosa.

In a separate study of adult patients with ulcerative colitis, who received balsalazide, 1.5 g twice daily, for over 1 year, systemic drug exposure, based on mean AUC values, was up to 60 times greater (0.008 mcg·hr/mL to 0.48 mcg·hr/mL) when compared to that obtained in healthy subjects who received the same dose.

Distribution

The binding of balsalazide to human plasma proteins was ≥99%.

Metabolism

The products of the azoreduction of this compound, 5-ASA and 4-aminobenzoyl-ß-alanine, and their N-acetylated metabolites have been identified in plasma, urine and feces.

Elimination

Following single-dose administration of 2.25 g balsalazide (three 750 mg capsules) under fasting conditions in healthy subjects, mean urinary recovery of balsalazide, 5-ASA, and N-Ac-5-ASA was 0.2%, 0.22% and 10.2%, respectively.

In a multiple-dose study in healthy subjects receiving a balsalazide dose of two 750 mg capsules twice daily (3 g/day) for 10 days, mean urinary recovery of balsalazide, 5-ASA, and N-Ac-5-ASA was 0.1%, 0%, and 11.3%, respectively. During this study, subjects received their morning dose 0.5 hours after being fed a standard meal, and subjects received their evening dose 2 hours after being fed a standard meal.

In a study with 10 healthy volunteers, 65% of a single 2.25 g dose of balsalazide was recovered as 5-ASA, 4-aminobenzoyl-ß-alanine, and the N-acetylated metabolites in feces, while <1% of the dose was recovered as parent compound.

In a study that examined the disposition of balsalazide in patients who were taking 3 to 6 g of balsalazide daily for more than 1 year and who were in remission from ulcerative colitis, less than 1% of an oral dose was recovered as intact balsalazide in the urine. Less than 4% of the dose was recovered as 5-ASA, while virtually no 4-aminobenzoyl-ß-alanine was detected in urine. The mean urinary recovery of N-Ac-5-ASA and N-acetyl-4-aminobenzoyl-ß-alanine comprised <16% and <12% of the balsalazide dose, respectively. No fecal recovery studies were performed in this population.

All pharmacokinetic studies with balsalazide are characterized by large variability in the plasma concentration versus time profiles for balsalazide and its metabolites, thus half-life estimates of these analytes are indeterminate.

13 NONCLINICAL TOXICOLOGY

13.1 Carcinogenesis, Mutagenesis, Impairment of Fertility

In a 24-month rat (Sprague Dawley) carcinogenicity study, oral (dietary) balsalazide disodium at doses up to 2 g/kg/day was not tumorigenic. For a 50 kg person of average height this dose represents 2.4 times the recommended human dose on a body surface area basis. Balsalazide disodium was not genotoxic in the following in vitro or in vivo tests: Ames test, human lymphocyte chromosomal aberration test, and mouse lymphoma cell (L5178Y/TK+/-) forward mutation test, or mouse micronucleus test. However, it was genotoxic in the in vitro Chinese hamster lung cell (CH V79/HGPRT) forward mutation test.

4-aminobenzoyl-ß-alanine, a metabolite of balsalazide disodium, was not genotoxic in the Ames test and the mouse lymphoma cell (L5178Y/TK+/-) forward mutation test but was positive in the human lymphocyte chromosomal aberration test. N-acetyl-4-aminobenzoyl-ß-alanine, a conjugated metabolite of balsalazide disodium, was not genotoxic in Ames test, the mouse lymphoma cell (L5178Y/TK+/-) forward mutation test, or the human lymphocyte chromosomal aberration test. Balsalazide disodium at oral doses up to 2 g/kg/day, 2.4 times the recommended human dose based on body surface area, was found to have no effect on fertility and reproductive performance in rats.

13.2 Animal Toxicology and/or Pharmacology

Renal Toxicity

In animal studies conducted at doses up to 2000 mg/kg (approximately 21 times the recommended 6.75 g/day dose on a mg/kg basis for a 70 kg person), balsalazide demonstrated no nephrotoxic effects in rats or dogs.

Overdosage

A single oral dose of balsalazide disodium at 5 g/kg or 4-aminobenzoyl-ß-alanine, a metabolite of balsalazide disodium, at 1 g/kg was non-lethal in mice and rats. No symptoms of acute toxicity were seen at these doses.

14 CLINICAL STUDIES

14.1 Adult Studies

Two randomized, double-blind studies were conducted in adults. In the first trial, 103 patients with active mild-to-moderate ulcerative colitis with sigmoidoscopy findings of friable or spontaneously bleeding mucosa were randomized and treated with balsalazide 6.75 g/day or balsalazide 2.25 g/day. The primary efficacy endpoint was reduction of rectal bleeding and improvement of at least one of the other assessed symptoms (stool frequency, patient functional assessment, abdominal pain, sigmoidoscopic grade, and physician’s global assessment [PGA]). Outcome assessment for rectal bleeding at each interim period (week 2, 4, and 8) encompassed a 4-day period (96 hours). Results demonstrated a statistically significant difference between high and low doses of balsalazide (Figure 1).

Figure 1: Percentage of Patients Improved at 8 Weeks

A second study, conducted in Europe, confirmed findings of symptomatic improvement.

16 HOW SUPPLIED/STORAGE AND HANDLING

Balsalazide Disodium Capsules are supplied as light orange opaque capsules containing 750 mg balsalazide disodium and "54 795" printed in black ink on the cap and body, containing a yellow-orange powder.

Bottles of 280 | NDC 54868-6137-0

Storage

Store at 20° to 25°C (68° to 77°F); excursions permitted between 15° to 30°C (59° to 86°F). [See USP Controlled Room Temperature.]

Roxane Laboratories, Inc.

Relabeling of "Additional" barcode label by:
Physicians Total Care, Inc.
Tulsa, OK 74146

17 PATIENT COUNSELING INFORMATION

17.1 Important Precautions Regarding Balsalazide

- Instruct patients not to take balsalazide if they have a hypersensitivity to salicylates (e.g., aspirin).
- Patients should be instructed to contact their health care provider under the following circumstances:
  - If they experience a worsening of their ulcerative colitis symptoms.
  - If they are diagnosed with pyloric stenosis, because balsalazide capsules may be slow to pass through their digestive tract.
  - If they are diagnosed with renal dysfunction. Damage to the kidney has been observed in people given medications similar to balsalazide.

17.2 What Patients Should Know About Adverse Reactions

- In adult clinical trials the most common adverse reactions were headache, abdominal pain, diarrhea, nausea, vomiting, respiratory infection, and arthralgia.
- Inform patients that this listing of adverse reactions is not complete and not all adverse reactions can be anticipated. If appropriate, a more comprehensive list of adverse reactions can be discussed with patients.

17.3 What Patients Should Know About Taking Balsalazide with Other Medication

- Based upon limited studies conducted in a test tube, balsalazide is not believed to interfere with other drugs by preventing how the liver functions. However, as the studies were limited in scope, you should always consult your doctor and discuss potential interactions prior to initiating any new drug.

10003708/04 Revised October 2010

©RLI, 2010

PRINCIPAL DISPLAY PANEL

Balsalazide Disodium Capsules, 750 mg

NDC 54868-6137-0